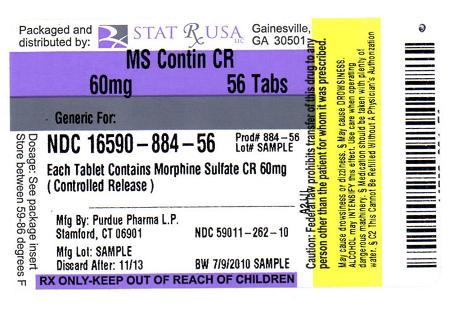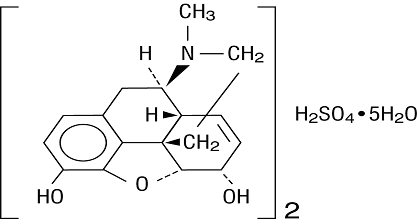 DRUG LABEL: MS CONTIN
NDC: 16590-884 | Form: TABLET, FILM COATED, EXTENDED RELEASE
Manufacturer: STAT RX USA LLC
Category: prescription | Type: HUMAN PRESCRIPTION DRUG LABEL
Date: 20100709
DEA Schedule: CII

ACTIVE INGREDIENTS: MORPHINE SULFATE 60 mg/1 1
INACTIVE INGREDIENTS: CETOSTEARYL ALCOHOL; HYDROXYETHYL CELLULOSE (140 CPS AT 5%); HYPROMELLOSES; MAGNESIUM STEARATE; POLYETHYLENE GLYCOL; TALC; TITANIUM DIOXIDE; LACTOSE; HYDROXYPROPYL CELLULOSE; D&C RED NO. 30; D&C YELLOW NO. 10

MS CONTIN® (morphine sulfate controlled-release) Tablets
CII 15 mg 30 mg 60 mg 100 mg* 200 mg*

BOXED WARNING

*100 mg and 200 mg are for use in opioid-tolerant patients only

WARNING:

MS CONTIN contains morphine sulfate, an opioid agonist and a Schedule II controlled substance, with an abuse liability similar to other opioid analgesics.

Morphine can be abused in a manner similar to other opioid agonists, legal or illicit. This should be considered when prescribing or dispensing MS CONTIN in situations where the physician or pharmacist is concerned about an increased risk of misuse, abuse, or diversion.

MS CONTIN Tablets are a controlled-release oral formulation of morphine sulfate indicated for the management of moderate to severe pain when a continuous, around-the-clock opioid analgesic is needed for an extended period of time.

MS CONTIN Tablets are NOT intended for use as a prn analgesic.

MS CONTIN 100 and 200 mg Tablets ARE FOR USE IN OPIOID-TOLERANT PATIENTS ONLY. These tablet strengths may cause fatal respiratory depression when administered to patients not previously exposed to opioids.

MS CONTIN TABLETS ARE TO BE SWALLOWED WHOLE AND ARE NOT TO BE BROKEN, CHEWED, DISSOLVED, OR CRUSHED. TAKING BROKEN, CHEWED, DISSOLVED, OR CRUSHED MS CONTIN TABLETS LEADS TO RAPID RELEASE AND ABSORPTION OF A POTENTIALLY FATAL DOSE OF MORPHINE.

DESCRIPTION

Chemically, morphine sulfate is 7,8-didehydro-4,5α-epoxy-17-methylmorphinan-3,6α-diol sulfate (2:1) (salt) pentahydrate and has the following structural formula:

MS CONTIN® (morphine sulfate controlled-release) Tablets are opiate analgesics supplied in 15, 30, 60, 100 and 200 mg tablet strengths. The tablet strengths describe the amount of morphine per tablet as the pentahydrated sulfate salt (morphine sulfate, USP). MS CONTIN® Controlled-release Tablets 15 mg, 30 mg, 60 mg, 100 mg, and 200 mg contain the following inactive ingredients: cetostearyl alcohol, hydroxyethyl cellulose, hypromellose, magnesium stearate, polyethylene glycol, talc and titanium dioxide.

MS CONTIN Controlled-release Tablets 15 mg also contains FD&C Blue No. 2, lactose and polysorbate 80.

MS CONTIN Controlled-release Tablets 30 mg also contains D&C Red No. 7, FD&C Blue No. 1, lactose and polysorbate 80.

MS CONTIN Controlled-release Tablets 60 mg also contains D&C Red No. 30, D&C Yellow No. 10, hydroxypropyl cellulose, and lactose.

MS CONTIN Controlled-release Tablets 100 mg also contains black iron oxide.

MS CONTIN Controlled-release Tablets 200 mg also contains D&C Yellow No. 10, FD&C Blue No. 1, and hydroxypropyl cellulose.

CLINICAL PHARMACOLOGY

Morphine is a pure opioid agonist whose principal therapeutic action is analgesia. Other members of the class known as opioid agonists include substances such as oxycodone, hydromorphone, fentanyl, codeine, and hydrocodone. Pharmacological effects of opioid agonists include anxiolysis, euphoria, feelings of relaxation, respiratory depression, constipation, miosis, cough suppression, and analgesia. Like all pure opioid agonist analgesics, with increasing doses there is increasing analgesia, unlike with mixed agonist/antagonists or non-opioid analgesics, where there is a limit to the analgesic effect with increasing doses. With pure opioid agonist analgesics, there is no defined maximum dose; the ceiling to analgesic effectiveness is imposed only by side effects, the more serious which may include somnolence and respiratory depression.

Central Nervous System

The principal actions of therapeutic value of morphine are analgesia and sedation (i.e., sleepiness and anxiolysis).

The precise mechanism of the analgesic action is unknown. However, specific CNS opiate receptors for endogenous compounds with opioid-like activity have been identified throughout the brain and spinal cord and are likely to play a role in the expression of analgesic effects.

Morphine produces respiratory depression by direct action on brainstem respiratory centers. The mechanism of respiratory depression involves a reduction in the responsiveness of the brainstem respiratory centers to increases in carbon dioxide tension, and to electrical stimulation.

Morphine depresses the cough reflex by direct effect on the cough center in the medulla. Antitussive effects may occur with doses lower than those usually required for analgesia. Morphine causes miosis, even in total darkness. Pinpoint pupils are a sign of narcotic overdose but are not pathognomonic (e.g., pontine lesions of hemorrhagic or ischemic origins may produce similar findings). Marked mydriasis rather than miosis may be seen with worsening hypoxia.

Gastrointestinal Tract and Other Smooth Muscle

Morphine causes a reduction in motility associated with an increase in smooth muscle tone in the antrum of the stomach and in the duodenum. Digestion of food is delayed in the small intestine and propulsive contractions are decreased. Propulsive peristaltic waves in the colon are decreased, while tone may be increased to the point of spasm resulting in constipation. Other opioid induced-effects may include a reduction in gastric, biliary and pancreatic secretions, spasm of the sphincter of Oddi, and transient elevations in serum amylase.

Cardiovascular System

Morphine produces peripheral vasodilation which may result in orthostatic hypotension. Release of histamine can occur and may contribute to opioid-induced hypotension. Manifestations of histamine release and/or peripheral vasodilation may include pruritus, flushing, red eyes, and sweating.

Endocrine System

Opioids have been shown to have a variety of effects on the secretion of hormones. Opioids inhibit the secretion of ACTH, cortisol, and luteinizing hormone (LH) in humans. They also stimulate prolactin, growth hormone (GH) secretion, and pancreatic secretion of insulin and glucagons in humans and other species, rats and dogs. Thyroid stimulating hormone (TSH) has been shown to be both inhibited and stimulated by opioids.

Immune System

Opioids have been shown to have a variety of effects on components of the immune system in in vitro and animal models. The clinical significance of these findings is unknown.

Pharmacodynamics

As with all opioids, the minimum effective plasma concentration for analgesia varies widely among patients, especially among patients who have been previously treated with potent agonist opioids. As a result, patients must be treated with individualized titration of dosage to the desired effect. The minimum effective analgesic concentration of morphine for any individual patient may increase over time due to an increase in pain, the development of new pain syndrome and/or the development of analgesic tolerance.

Plasma Level-Analgesia Relationships

In any particular patient, both analgesic effects and plasma morphine concentrations are related to the morphine dose. In non-tolerant individuals, plasma morphine concentration-efficacy relationships have been demonstrated and suggest that opiate receptors occupy effector compartments, leading to a lag-time, or hysteresis, between rapid changes in plasma morphine concentrations and the effects of such changes. The most direct and predictable concentration-effect relationships can, therefore, be expected at distribution equilibrium and/or steady-state conditions.

While plasma morphine-efficacy relationships can be demonstrated in non-tolerant individuals, they are influenced by a wide variety of factors and are not generally useful as a guide to the clinical use of morphine. The effective dose in opioid-tolerant patients may be significantly greater than the appropriate dose for opioid-naive individuals. Dosages of morphine should be chosen and must be titrated on the basis of clinical evaluation of the patient and the balance between therapeutic and adverse effects.

For any fixed dose and dosing interval, MS CONTIN will have at steady-state, a lower Cmax and a higher Cmin than conventional morphine.

Concentration - Adverse Experience Relationships

MS CONTIN® Tablets are associated with typical opioid-related adverse experiences. There is a general relationship between increasing morphine plasma concentration and increasing frequency of dose-related opioid adverse experiences such as nausea, vomiting, CNS effects, and respiratory depression. In opioid-tolerant patients, the situation is altered by the development of tolerance to opioid-related side effects, and the relationship is not clinically relevant.

As with all opioids, the dose must be individualized (see DOSAGE AND ADMINISTRATION), because the effective analgesic dose for some patients will be too high to be tolerated by other patients.

PHARMACOKINETICS AND METABOLISM

MS CONTIN is a controlled-release tablet containing morphine sulfate. Morphine is released from MS CONTIN somewhat more slowly than from immediate-release oral preparations. Following oral administration of a given dose of morphine, the amount ultimately absorbed is essentially the same whether the source is MS CONTIN or an immediate-release formulation. Because of pre-systemic elimination (i.e., metabolism in the gut wall and liver) only about 40% of the administered dose reaches the central compartment.

Variation in the physical/mechanical properties of a formulation of an oral morphine drug product can affect both its absolute bioavailability and its absorption rate constant (ka). The formulation employed in MS CONTIN has not been shown to affect morphine's oral bioavailability, but does decrease its apparent ka. Other basic pharmacokinetic parameters (e.g., volume of distribution [Vd], elimination rate constant [ke], clearance [Cl]), are unchanged as they are fundamental properties of morphine in the organism. However, in chronic use, the possibility that shifts in metabolite to parent drug ratios may occur cannot be excluded.

When immediate-release oral morphine or MS CONTIN is given on a fixed dosing regimen, steady-state is achieved in about a day.

For a given dose and dosing interval, the AUC and average blood concentration of morphine at steady-state (Css) will be independent of the specific type of oral formulation administered so long as the formulations have the same absolute bioavailability. The absorption rate of a formulation will, however, affect the maximum (Cmax) and minimum (Cmin) blood levels and the times of their occurrence.

Absorption

Following the administration of immediate-release oral morphine products, approximately fifty percent of the morphine that will reach the central compartment intact reaches it within 30 minutes. Following the administration of an equal amount of MS CONTIN to normal volunteers, however, this extent of absorption occurs, on average, after 1.5 hours.

Food Effects

The possible effect of food upon the systemic bioavailability of MS CONTIN® has not been systematically evaluated for all strengths. One study, conducted with the 30 mg MS CONTIN Tablets, showed no significant differences in Cmax and AUC (0-24h) values, whether the tablet was taken while fasting or with a high-fat breakfast.

Distribution

The volume of distribution (Vd) for morphine is approximately 4 liters per kilogram. Once absorbed, morphine is distributed to skeletal muscle, kidneys, liver, intestinal tract, lungs, spleen, and brain. Morphine also crosses the placental membranes and has been found in breast milk.

Metabolism

Although a small fraction (less than 5%) of morphine is demethylated, for all practical purposes, virtually all morphine is converted to the 3- and 6- (M3G and M6G) glucuronide metabolites. M3G is present in the highest plasma concentration following oral administration and possesses no significant analgesic activity. M6G, while possessing analgesic activity, is present in the plasma in low concentrations.

Excretion

The elimination of morphine occurs primarily as renal excretion of morphine-3- glucuronide and its terminal elimination half-life after intravenous administration is normally 2 to 4 hours. In some studies involving longer periods of plasma sampling, a longer terminal half-life of about 15 hours was reported. A small amount of the glucuronide conjugate is excreted in the bile, and there is some minor enterohepatic recycling. As with any drug, caution should be taken to guard against unanticipated accumulation if renal and/or hepatic function is seriously impaired.

Special Populations

Renal Impairment

Morphine pharmacokinetics are altered in patients with renal failure. Clearance is decreased and the metabolites, M3G and M6G, may accumulate to much higher plasma levels in these patients as compared to patients with normal renal function.

Drug-Drug Interactions

Known drug-drug interactions involving morphine are pharmacodynamic not pharmacokinetic.

INDICATIONS AND USAGE

MS CONTIN Tablets are a controlled-release oral formulation of morphine sulfate indicated for the management of moderate to severe pain when a continuous, around-the-clock opioid analgesic is needed for an extended period of time.

MS CONTIN Tablets are NOT intended for use as a prn analgesic.

The MS CONTIN 100 and 200 mg tablet strengths are high dose, controlled-release, oral morphine formulations indicated for the relief of pain in opioid-tolerant patients only.

MS CONTIN is not indicated for pain in the immediate postoperative period (the first 12-24 hours following surgery) for patients not previously taking the drug, because its safety in this setting has not been established.

MS CONTIN is not indicated for pain in the postoperative period if the pain is mild, or not expected to persist for an extended period of time.

MS CONTIN is only indicated for postoperative use if the patient is already receiving the drug prior to surgery or if the postoperative pain is expected to be moderate to severe and persist for an extended period of time. Physicians should individualize treatment, moving from parenteral to oral analgesics as appropriate. (See American Pain Society guidelines.)

CONTRAINDICATIONS

MS CONTIN is contraindicated in patients with known hypersensitivity to morphine or in any situation where opioids are contraindicated. This includes patients with respiratory depression (in the absence of resuscitative equipment or in unmonitored settings), and in patients with acute or severe bronchial asthma or hypercarbia.

MS CONTIN is contraindicated in any patient who has or is suspected of having a paralytic ileus.

WARNINGS

(See also:CLINICAL PHARMACOLOGY)

MS CONTIN (MORPHINE SULFATE CONTROLLED-RELEASE) TABLETS ARE TO BE SWALLOWED WHOLE AND ARE NOT TO BE BROKEN, CHEWED, DISSOLVED, OR CRUSHED. TAKING BROKEN, CHEWED, DISSOLVED, OR CRUSHED MS CONTIN® TABLETS LEADS TO RAPID RELEASE AND ABSORPTION OF A POTENTIALLY FATAL DOSE OF MORPHINE.

MS CONTIN 100 AND 200 mg Tablets ARE FOR USE IN OPIOID-TOLERANT PATIENTS ONLY. These tablet strengths may cause fatal respiratory depression when administered to patients not previously exposed to opioids.

MS CONTIN 100 AND 200 mg Tablets are for use only in opioid-tolerant patients requiring daily morphine equivalent dosages of 200 mg or more for the 100 mg tablet and 400 mg or more for the 200 mg tablet. Care should be taken in the prescribing of these tablet strengths. Patients should be instructed against use by individuals other than the patient for whom it was prescribed, as such inappropriate use may have severe medical consequences, including death.

Misuse, Abuse and Diversion of Opioids

Morphine is an opioid agonist and a Schedule II controlled substance. Such drugs are sought by drug abusers and people with addiction disorders and are subject to criminal diversion.

Morphine can be abused in a manner similar to other opioid agonists, legal or illicit. This should be considered when prescribing or dispensing MS CONTIN® in situations where the physician or pharmacist is concerned about an increased risk of misuse, abuse, or diversion.

MS CONTIN can be abused by crushing, chewing, snorting or injecting the dissolved product. These practices will result in the uncontrolled delivery of the opioid and pose a significant risk to the abuser that could result in overdose and death (see WARNINGS: Drug Abuse and Addiction).

Concerns about abuse, addiction, and diversion should not prevent the proper management of pain.

Healthcare professionals should contact their State Professional Licensing Board, or State Controlled Substances Authority for information on how to prevent and detect abuse or diversion of this product.

Interactions with Alcohol and Drugs of Abuse

Morphine may be expected to have additive effects when used in conjunction with alcohol, other opioids, or illicit drugs that cause central nervous system depression because respiratory depression, hypotension, and profound sedation or coma may result. (See WARNINGS: Interactions with other CNS Depressants.)

Drug Abuse and Addiction

MS CONTIN is a mu-agonist opioid with an abuse liability similar to other opioid agonists and is a Schedule II controlled substance. MS CONTIN and other opioids used in analgesia, can be abused and are subject to criminal diversion.

Drug addiction is characterized by compulsive use, use for non-medical purposes, and continued use despite harm or risk of harm. Drug addiction is a treatable disease, utilizing a multi-disciplinary approach, but relapse is common.

“Drug-seeking” behavior is very common in addicts and drug abusers. Drug-seeking tactics include emergency calls or visits near the end of office hours, refusal to undergo appropriate examination, testing or referral, repeated “loss” of prescriptions, tampering with prescriptions and reluctance to provide prior medical records or contact information for other treating physician(s). “Doctor shopping” to obtain additional prescriptions is common among drug abusers and people suffering from untreated addiction.

Abuse and addiction are separate and distinct from physical dependence and tolerance. Physicians should be aware that addiction may not be accompanied by concurrent tolerance and symptoms of physical dependence in all addicts. In addition, abuse of opioids can occur in the absence of true addiction and is characterized by misuse for non-medical purposes, often in combination with other psychoactive substances. MS CONTIN, like other opioids, has been diverted for non-medical use. Careful record keeping of prescribing information, including quantity, frequency, and renewal requests is strongly advised.

Proper assessment of the patient, proper prescribing practices, periodic re-evaluation of therapy, and proper dispensing and storage are appropriate measures that help to limit abuse of opioid drugs.

MS CONTIN is intended for oral use only as an intact tablet. Abuse of the crushed tablet poses a hazard of overdose and death. This risk is increased with concurrent abuse of alcohol and other substances. Due to the presence of talc as one of the excipients in tablets, parenteral abuse can be expected to result in local tissue necrosis, infection, pulmonary granulomas, and increased risk of endocarditis and valvular heart injury. Parenteral drug abuse is commonly associated with transmission of infectious diseases such as hepatitis and HIV.

Respiratory Depression

Respiratory depression is the chief hazard of all morphine preparations. Respiratory depression occurs most frequently in the elderly and debilitated patients as well as in those suffering from conditions accompanied by hypoxia or hypercapnia when even moderate therapeutic doses may dangerously decrease pulmonary ventilation.

Morphine should be used with extreme caution in patients with chronic obstructive pulmonary disease or cor pulmonale, and in patients having a substantially decreased respiratory reserve, hypoxia, hypercapnia, or pre-existing respiratory depression. In such patients, even usual therapeutic doses of morphine may decrease respiratory drive while simultaneously increasing airway resistance to the point of apnea.

Head Injury and Increased Intracranial Pressure

The respiratory depressant effects of morphine with carbon dioxide retention and secondary elevation of cerebrospinal fluid pressure may be markedly exaggerated in the presence of head injury, other intracranial lesions, or pre-existing increase in intracranial pressure. Morphine produces effects which may obscure neurologic signs of further increases in pressure in patients with head injuries.

Hypotensive Effect

MS CONTIN®, like all opioid analgesics, may cause severe hypotension in an individual whose ability to maintain his blood pressure has already been compromised by a depleted blood volume, or a concurrent administration of drugs such as phenothiazines or general anesthetics. MS CONTIN may produce orthostatic hypotension in ambulatory patients.

MS CONTIN, like all opioid analgesics, should be administered with caution to patients in circulatory shock, since vasodilation produced by the drug may further reduce cardiac output and blood pressure.

Interactions with other CNS Depressants

MS CONTIN, like all opioid analgesics, should be used with great caution and in reduced dosage in patients who are concurrently receiving other central nervous system depressants including sedatives or hypnotics, general anesthetics, phenothiazines, other tranquilizers, and alcohol because respiratory depression, hypotension, and profound sedation or coma may result.

Other

Although extremely rare, cases of anaphylaxis have been reported.

PRECAUTIONS

(See also: CLINICAL PHARMACOLOGY)

Special precautions regarding MS CONTIN 100 mg and 200 mg Tablets

MS CONTIN 100 mg and 200 mg Tablets are for use only in opioid-tolerant patients requiring daily morphine equivalent dosages of 200 or more for the 100 mg tablet and 400 mg or more for the 200 mg tablet. Care should be taken in its prescription and patients should be instructed against use by individuals other than the patient for whom it was prescribed, as this may have severe medical consequences for that individual.

General

MS CONTIN Tablets are a controlled-release oral formulation of morphine sulfate indicated for the management of moderate to severe pain when a continuous, around-the-clock analgesic is needed for an extended period of time. MS CONTIN does not release morphine continuously over the course of a dosing interval. The administration of single doses of MS CONTIN on a q12h dosing schedule will result in higher peak and lower trough plasma levels than those that occur when an identical daily dose of morphine is administered using conventional oral formulations on a q4h regimen. The clinical significance of greater fluctuations in morphine plasma level has not been systematically evaluated. (See DOSAGE AND ADMINISTRATION.)

Selection of patients for treatment with MS CONTIN® should be governed by the same principles that apply to the use of morphine or other potent opioid analgesics. Specifically, the increased risks associated with its use in the following populations should be considered: the elderly or debilitated and those with severe impairment of hepatic, pulmonary, or renal function; myxedema or hypothyroidism; adrenocortical insufficiency (e.g., Addison's Disease); CNS depression or coma; toxic psychosis; prostatic hypertrophy or urethral stricture; acute alcoholism; delirium tremens; kyphoscoliosis or inability to swallow.

The administration of morphine, like all opioid analgesics, may obscure the diagnosis or clinical course in patients with acute abdominal conditions.

Morphine may aggravate convulsions in patients with convulsive disorders, and all opioids may induce or aggravate seizures in some clinical settings.

Interactions with Mixed Agonist/Antagonist Opioid Analgesics

Agonist/antagonist analgesics (i.e., pentazocine, nalbuphine, and butorphanol) should be administered with caution to a patient who has received or is receiving a course of therapy with a pure opioid agonist analgesic such as morphine sulfate. In this situation, mixed agonist/antagonist analgesics may reduce the analgesic effect of morphine sulfate and/or may precipitate withdrawal symptoms in these patients.

Use in Pancreatic/Biliary Tract Disease

Morphine should be used with caution in patients about to undergo surgery of the biliary tract since it may cause spasm of the sphincter of Oddi. Similarly, morphine should be used with caution in patients with acute pancreatitis secondary to biliary tract disease.

Tolerance

Tolerance is a state of adaptation in which exposure to a drug induces changes that result in a diminution of one or more of the drug’s effects over time. Tolerance may occur to both the desired and undesired effects of drugs, and may develop at different rates for different effects.

Physical Dependence

Physical dependence is a state of adaptation that is manifested by an opioid specific withdrawal syndrome that can be produced by abrupt cessation, rapid dose reduction, decreasing blood level of the drug, and/or administration of an antagonist.

The opioid abstinence or withdrawal syndrome is characterized by some or all of the following: restlessness, lacrimation, rhinorrhea, yawning, perspiration, chills, piloerection, myalgia, mydriasis, irritability, anxiety, backache, joint pain, weakness, abdominal cramps, insomnia, nausea, anorexia, vomiting, diarrhea, or increased blood pressure, respiratory rate, or heart rate.

In general, opioids should not be abruptly discontinued (see DOSAGE AND ADMINISTRATION: Cessation of Therapy).

Information for Patients/Caregivers

If clinically advisable, patients receiving MS CONTIN® or their caregivers should be given the following information by the physician, nurse, or pharmacist:

1. Patients should be advised that MS CONTIN Tablets contain morphine and should be taken only as directed.
2. Patients should be advised that MS CONTIN Tablets were designed to work properly only if swallowed whole. MS CONTIN Tablets will release all of their morphine if split, divided, broken, chewed, dissolved, or crushed resulting in the risk of a fatal overdose.
3. Patients should be advised not to change the dose of MS CONTIN without consulting their physician.
4. Patients should be advised to report episodes of breakthrough pain and adverse experiences occurring during therapy. Individualization of dosage is essential to make optimal use of this medication.
5. MS CONTIN may impair mental and/or physical ability required for the performance of potentially hazardous tasks (e.g., driving, operating machinery). Patients started on MS CONTIN or whose dose has been changed should refrain from dangerous activity until it is established that they are not adversely affected.
6. MS CONTIN should not be taken with alcohol or other CNS depressants (sleep aids, tranquilizers) except by the orders of the prescribing physician because dangerous additive effects may occur resulting in serious injury or death.
7. Women of childbearing potential who become or are planning to become pregnant should be advised to consult their physician regarding the effects of analgesics and other drug use during pregnancy on themselves and their unborn child.
8. Patients should be advised that if they have been receiving treatment with MS CONTIN for more than a few weeks and cessation of therapy is indicated, it may be appropriate to taper the MS CONTIN dose, rather than abruptly discontinue it, due to the risk of precipitating withdrawal symptoms. Their physician can provide a dose schedule to accomplish a gradual discontinuation of the medication.
9. MS CONTIN® 100 mg and 200 mg Tablets are for use only in opioid-tolerant patients requiring daily morphine equivalent dosages of 200 mg or more for the 100 mg tablet and 400 mg or more for the 200 mg tablet. Special care must be taken to avoid accidental ingestion or the use by individuals (including children) other than the patient for whom it was originally prescribed, as such unsupervised use may have severe, even fatal, consequences.
10. Patients should be advised that MS CONTIN® is a potential drug of abuse. They should protect it from theft, and it should never be given to anyone other than the individual for whom it was prescribed.
11. Patients should be advised that they may pass empty matrix "ghosts" (tablets) via colostomy or in the stool, and that this is of no concern since the active medication has already been absorbed.
12. Patients should be instructed to keep MS CONTIN in a secure place out of the reach of children. When MS CONTIN is no longer needed, the unused tablets should be destroyed by flushing down the toilet.

Use in Drug and Alcohol Addiction

MS CONTIN is an opioid with no approved use in the management of addiction disorders. Its proper usage in individuals with drug or alcohol dependence, either active or in remission, is for the management of pain requiring opioid analgesia.

LABORATORY TESTS

Drug Interactions (See also: WARNINGS)

Use with CNS Depressants

The concomitant use of other central nervous system depressants including sedatives or hypnotics, general anesthetics, phenothiazines, tranquilizers, and alcohol may produce additive depressant effects. Respiratory depression, hypotension, and profound sedation or coma may occur. When such combined therapy is contemplated, the dose of one or both agents should be reduced. Opioid analgesics, including MS CONTIN, may enhance the neuromuscular blocking action of skeletal muscle relaxants and produce an increased degree of respiratory depression.

Carcinogenicity/Mutagenicity/Impairment of Fertility

Studies of morphine sulfate in animals to evaluate the drug's carcinogenic and mutagenic potential or the effect on fertility have not been conducted.

Pregnancy

Teratogenic Effects - CATEGORY C

Adequate animal studies on reproduction have not been performed to determine whether morphine affects fertility in males or females. There are no well-controlled studies in women, but marketing experience does not include any evidence of adverse effects on the fetus following routine (short-term) clinical use of morphine sulfate products. Although there is no clearly defined risk, such experience cannot exclude the possibility of infrequent or subtle damage to the human fetus.

MS CONTIN® should be used in pregnant women only if the need for strong opioid analgesia clearly outweighs the potential risk to the fetus. (See also: PRECAUTIONS: Labor and Delivery, and WARNINGS: Drug Abuse and Addiction.)

Labor and Delivery

MS CONTIN is not recommended for use in women during and immediately prior to labor. Occasionally, opioid analgesics may prolong labor through actions which temporarily reduce the strength, duration, and frequency of uterine contractions. However, this effect is not consistent and may be offset by an increased rate of cervical dilatation which tends to shorten labor.

Neonates whose mothers received opioid analgesics during labor should be observed closely for signs of respiratory depression. A specific narcotic antagonist, naloxone, should be available for reversal of narcotic-induced respiratory depression in the neonate.

Neonatal Withdrawal Syndrome

Chronic maternal use of opioids during pregnancy can affect the fetus with subsequent withdrawal symptoms. Neonatal withdrawal syndrome presents as irritability, hyperactivity and abnormal sleep pattern, abnormal crying, tremor, vomiting, diarrhea and subsequent weight loss or failure to gain weight, and may result in death. The onset, duration and severity of neonatal withdrawal syndrome varies based on the drug used, duration of use, the and dose of last maternal use, and rate of elimination by the newborn. Use standard care as medically appropriate.

Nursing Mothers

Low levels of morphine have been detected in the breast milk. Withdrawal symptoms can occur in breast-feeding infants when maternal administration of morphine sulfate is stopped. Ordinarily, nursing should not be undertaken while a patient is receiving MS CONTIN since morphine may be excreted in the milk.

Pediatric Use

Safety and effectiveness in pediatric patients have not been established.

MS CONTIN Tablets are not to be chewed, crushed, dissolved or divided for administration.

Geriatric Use

Clinical studies of MS CONTIN did not include sufficient numbers of subjects aged 65 and over to determine whether they respond differently from younger subjects. Other reported clinical experience has not identified differences in responses between the elderly and younger patients. In general, dose selection for an elderly patient should be cautious, usually starting at the low end of the dosing range, reflecting the greater frequency of decreased hepatic, renal, or cardiac function, and of concomitant disease or other drug therapy.

ADVERSE REACTIONS

The adverse reactions caused by morphine are essentially those observed with other opioid analgesics. They include the following major hazards: respiratory depression, apnea, and to a lesser degree, circulatory depression, respiratory arrest, shock, and cardiac arrest.

Most Frequently Observed

Constipation, lightheadedness, dizziness, sedation, nausea, vomiting, sweating, dysphoria, and euphoria.

Some of these effects seem to be more prominent in ambulatory patients and in those not experiencing severe pain. Some adverse reactions in ambulatory patients may be alleviated if the patient lies down.

Less Frequently Observed Reactions

Central Nervous System: Weakness, headache, agitation, tremor, uncoordinated muscle movements, seizure, alterations of mood (nervousness, apprehension, depression, floating feelings), dreams, muscle rigidity, transient hallucinations and disorientation, visual disturbances, insomnia, increased intracranial pressure

Gastrointestinal: Dry mouth, biliary tract spasm, laryngospasm, anorexia, diarrhea, cramps, taste alteration, constipation, ileus, intestinal obstruction, dyspepsia, increases in hepatic enzymes

Cardiovascular: Flushing of the face, chills, tachycardia, bradycardia, palpitation, faintness, syncope, hypotension, hypertension

Genitourinary: Urine retention or hesitance, amenorrhea, reduced libido and/or potency

Dermatologic: Pruritus, urticaria, other skin rashes, edema, diaphoresis

Other: Antidiuretic effect, paresthesia, bronchospasm, muscle tremor, blurred vision, nystagmus, diplopia, miosis, anaphylaxis, malaise, thinking disturbances, vertigo

OVERDOSAGE

Acute overdosage with morphine can be manifested by respiratory depression, somnolence progressing to stupor or coma, skeletal muscle flaccidity, cold and clammy skin, constricted pupils, rhabdomyolysis progressing to renal failure, and, sometimes, bradycardia, hypotension and death.

The nature of the controlled-release morphine should also be taken into account when treating the overdose. Even in the face of improvement, continued medical monitoring is required because of the possibility of extended effects. Deaths due to overdose may occur with abuse and misuse of MS CONTIN Tablets.

In the treatment of morphine overdosage, primary attention should be given to the re-establishment of a patent airway and institution of assisted or controlled ventilation. Supportive measures (including oxygen, vasopressors) should be employed in the management of circulatory shock and pulmonary edema accompanying overdose as indicated. Cardiac arrest or arrhythmias may require cardiac massage or defibrillation.

The pure opioid antagonists, such as naloxone, are specific antidotes against respiratory depression which results from opioid overdose. Naloxone should be administered intravenously; however, because its duration of action is relatively short, the patient must be carefully monitored until spontaneous respiration is reliably re-established. If the response to naloxone is suboptimal or not sustained, additional naloxone may be administered, as needed, or given by continuous infusion to maintain alertness and respiratory function; however, there is no information available about the cumulative dose of naloxone that may be safely administered.

Opioid antagonists should not be administered in the absence of clinically significant respiratory or circulatory depression secondary to morphine overdose. Such agents should be administered cautiously to persons who are known, or suspected to be physically-dependent on MS CONTIN®. In such cases, an abrupt or complete reversal of opioid effects may precipitate an acute abstinence syndrome.

Note: In an individual physically dependent on opioids, administration of the usual dose of the antagonist will precipitate an acute withdrawal syndrome. The severity of the withdrawal syndrome produced will depend on the degree of physical dependence and the dose of the antagonist administered. Use of an opioid antagonist in such a person should be avoided. If necessary to treat serious respiratory depression in the physically dependent patient, the antagonist should be administered with care and by titration with smaller than usual doses of the antagonist.

DOSAGE AND ADMINISTRATION

(SEE ALSO: CLINICAL PHARMACOLOGY, WARNINGS, AND PRECAUTIONS SECTIONS)

MS CONTIN IS AN OPIOID AGONIST AND A SCHEDULE II CONTROLLED SUBSTANCE WITH AN ABUSE LIABILITY SIMILAR TO OTHER OPIOID AGONISTS. MORPHINE AND OTHER OPIOIDS USED IN ANALGESIA CAN BE ABUSED AND ARE SUBJECT TO CRIMINAL DIVERSION.

MS CONTIN TABLETS ARE TO BE SWALLOWED WHOLE, AND ARE NOT TO BE BROKEN, CHEWED, DISSOLVED OR CRUSHED. TAKING BROKEN, CHEWED, DISSOLVED, OR CRUSHED MS CONTIN TABLETS LEADS TO RAPID RELEASE AND ABSORPTION OF A POTENTIALLY FATAL DOSE OF MORPHINE.

Physicians should individualize treatment in every case, initiating therapy at the appropriate point along a progression from non-opioid analgesics, such as non-steroidal anti-inflammatory drugs and acetaminophen to opioids in a plan of pain management such as those outlined by the World Health Organization, the Federation of State Medical Boards Model Guidelines, or the American Pain Society. Healthcare professionals should follow appropriate pain management principles of careful assessment and ongoing monitoring (see BOXED WARNING).

MS CONTIN® Tablets are a controlled-release oral formulation of morphine sulfate indicated for the management of moderate to severe pain when a continuous, around-the-clock analgesic is needed for an extended period of time. The controlled-release nature of the formulation allows it to be administered on a more convenient schedule than conventional immediate-release oral morphine products. (See CLINICAL PHARMACOLOGY; PHARMACOKINETICS AND METABOLISM.) However, MS CONTIN does not release morphine continuously over the course of a dosing interval. The administration of single doses of MS CONTIN on a q12h dosing schedule will result in higher peak and lower trough plasma levels than those that occur when an identical daily dose of morphine is administered using conventional oral formulations on a q4h regimen. The clinical significance of greater fluctuations in morphine plasma level has not been systematically evaluated.

As with any potent opioid drug product, it is critical to adjust the dosing regimen for each patient individually, taking into account the patient's prior opioid and non-opioid analgesic treatment experience. Although it is clearly impossible to enumerate every consideration that is important to the selection of initial dose and dosing interval of MS CONTIN, attention should be given to 1) the daily dose, potency, and precise characteristics of the opioid the patient has been taking previously (e.g., whether it is a pure agonist or mixed agonist/antagonist), 2) the reliability of the relative potency estimate used to calculate the dose of morphine needed [N.B. potency estimates may vary with the route of administration], 3) the degree of opioid tolerance, if any, and 4) the general condition and medical status of the patient.

The following dosing recommendations, therefore, can only be considered suggested approaches to what is actually a series of clinical decisions in the management of the pain of an individual patient.

During periods of changing analgesic requirements including initial titration, frequent contact is recommended between physician, other members of the healthcare team, the patient, and the caregiver/family.

Conversion from Immediate-Release Oral Morphine to MS CONTIN

A patient's daily morphine requirement is established using immediate-release oral morphine (dosing every 4 to 6 hours). The patient is then converted to MS CONTIN® in either of two ways: 1) by administering one-half of the patient's 24-hour requirement as MS CONTIN on an every 12-hour schedule; or, 2) by administering one-third of the patient's daily requirement as MS CONTIN on an every eight hour schedule. With either method, dose and dosing interval is then adjusted as needed (see discussion below). The 15 mg tablet should be used for initial conversion for patients whose total daily requirement is expected to be less than 60 mg. The 30 mg tablet strength is recommended for patients with a daily morphine requirement of 60 to 120 mg. When the total daily dose is expected to be greater than 120 mg, the appropriate combination of tablet strengths should be employed.

Conversion from Parenteral Morphine or Other Opioids (Parenteral or Oral) to MS CONTIN

MS CONTIN can be administered as the initial oral morphine drug product; in this case, however, particular care must be exercised in the conversion process. Because of uncertainty about, and intersubject variation in, relative estimates of opioid potency and cross tolerance, initial dosing regimens should be conservative. It is better to underestimate the 24-hour oral morphine requirement than to overestimate. To this end, initial individual doses of MS CONTIN should be estimated conservatively. In patients whose daily morphine requirements are expected to be less than or equal to 120 mg per day, the 30 mg tablet strength is recommended for the initial titration period. Once a stable dose regimen is reached, the patient can be converted to the 60 mg or 100 mg tablet strength, or an appropriate combination of tablet strengths, if desired.

Estimates of the relative potency of opioids are only approximate and are influenced by route of administration, individual patient differences, and possibly, by an individual's medical condition. Consequently, it is difficult to recommend any fixed rule for converting a patient to MS CONTIN directly. The following general points should be considered, however.

1. Parenteral to oral morphine ratio: Estimates of the oral to parenteral potency of morphine vary. Some authorities suggest that a dose of oral morphine only three times the daily parenteral morphine requirement may be sufficient in chronic use settings.
2. Other parenteral or oral opioids to oral morphine: Because there is lack of systematic evidence bearing on these types of analgesic substitutions, specific recommendations are not possible.

Physicians are advised to refer to published relative potency data, keeping in mind that such ratios are only approximate. In general, it is safer to underestimate the daily dose of MS CONTIN required and rely upon ad hoc supplementation to deal with inadequate analgesia. (See discussion which follows.)

Use of MS CONTIN as the First Opioid Analgesic

There has been no systematic evaluation of MS CONTIN as an initial opioid analgesic in the management of pain. Because it may be more difficult to titrate a patient using a controlled-release morphine, it is ordinarily advisable to begin treatment using an immediate-release formulation. (See Special Instructions for MS CONTIN® 100 and 200 mg Tablets)

Considerations in the Adjustment of Dosing Regimens

Whatever the approach, if signs of excessive opioid effects are observed early in a dosing interval, the next dose should be reduced. If this adjustment leads to inadequate analgesia, that is, "breakthrough" pain occurs late in the dosing interval, the dosing interval may be shortened. Alternatively, a supplemental dose of a short-acting analgesic may be given. As experience is gained, adjustments can be made to obtain an appropriate balance between pain relief, opioid side effects, and the convenience of the dosing schedule.

In adjusting dosing requirements, it is recommended that the dosing interval never be extended beyond 12 hours because the administration of very large single doses may lead to acute overdose. (N.B. MS CONTIN is a controlled-release formulation; it does not release morphine continuously over the dosing interval.)

For patients with low daily morphine requirements, the 15 mg tablet should be used.

Special Instructions for MS CONTIN 100 and 200 mg Tablets
(For use in opioid-tolerant patients only.)

MS CONTIN 100 mg and 200 mg tablets are for use only in opioid-tolerant patients requiring daily morphine equivalent dosages of 200 mg or more for the 100 mg tablet and 400 mg or more for the 200 mg tablet. It is recommended that these strengths be reserved for patients that have already been titrated to a stable analgesic regimen using lower strengths of MS CONTIN or other opioids.

Supplemental Analgesia

Most patients given around-the-clock therapy with controlled-release opioids may need to have immediate-release medication available for exacerbations of pain or to prevent pain that occurs predictably during certain patient activities (including incident pain).

Continuation of Therapy

The intent of the titration period is to establish a patient-specific daily dose that will provide adequate analgesia with acceptable side effects and minimal rescue doses (2 or less) for as long as pain relief is necessary. Should pain recur, the dose can be increased to re-establish pain control as outlined above. During chronic, around-the-clock opioid therapy, especially for non-cancer pain syndromes, the continued need for around-the-clock opioid therapy should be reassessed periodically (e.g. every 6 to 12 months) as appropriate.

Cessation of Therapy

When the patient no longer requires therapy with MS CONTIN® tablets, doses should be tapered gradually to prevent signs and symptoms of withdrawal in the physically dependent patient.

Conversion from MS CONTIN to Parenteral Opioids

When converting a patient from MS CONTIN to parenteral opioids, it is best to assume that the parenteral to oral potency is high. NOTE THAT THIS IS THE CONVERSE OF THE STRATEGY USED WHEN THE DIRECTION OF CONVERSION IS FROM THE PARENTERAL TO ORAL FORMULATIONS. IN BOTH CASES, HOWEVER, THE AIM IS TO ESTIMATE THE NEW DOSE CONSERVATIVELY. For example, to estimate the required 24-hour dose of morphine for IM use, one could employ a conversion of 1 mg of morphine IM for every 6 mg of morphine as MS CONTIN. The IM 24-hour dose would have to be divided by six and administered on a q4h regimen. This approach is recommended because it is least likely to cause overdose.

SAFETY AND HANDLING

MS CONTIN Tablets contain morphine sulfate which is a controlled substance under Schedule II of the Controlled Substances Act. Morphine, like all opioids, is liable to diversion and misuse and should be handled accordingly. Patients and their families should be instructed to flush any unneeded MS CONTIN tablets down the toilet.

MS CONTIN may be targeted for theft and diversion by criminals. Healthcare professionals should contact their State Professional Licensing Board or State Controlled Substances Authority for information on how to prevent and detect abuse or diversion of this product.

MS CONTIN TABLETS ARE TO BE SWALLOWED WHOLE, AND ARE NOT TO BE BROKEN, CHEWED, DISSOLVED, OR CRUSHED. TAKING BROKEN, CHEWED, DISSOLVED, OR CRUSHED MS CONTIN TABLETS LEADS TO RAPID RELEASE AND ABSORPTION OF A POTENTIALLY FATAL DOSE OF MORPHINE.

MS CONTIN 100 mg and 200 mg tablets are for use only in opioid-tolerant patients requiring daily morphine equivalent dosages of 200 mg or more for the 100 mg tablet and 400 mg or more for the 200 mg tablet. This strength is potentially fatal if accidentally ingested and patients and their families should be instructed to take special care to avoid accidental or intentional ingestion by individuals other than those for whom the medication was originally prescribed.

HOW SUPPLIED

MS CONTIN® (morphine sulfate controlled-release) Tablets 15 mg are round, blue-colored, film-coated tablets bearing the symbol PF on one side and M 15 on the other. They are supplied as follows:

NDC 59011-260-10: opaque plastic bottles containing 100 tablets
NDC 59011-260-05: opaque plastic bottles containing 500 tablets

MS CONTIN® (morphine sulfate controlled-release) Tablets 30 mg are round, lavender-colored, film-coated tablets bearing the symbol PF on one side and M 30 on the other. They are supplied as follows:

NDC 59011-261-25: opaque plastic bottles containing 100 tablets
NDC 59011-261-05: opaque plastic bottles containing 500 tablets

MS CONTIN® (morphine sulfate controlled-release) Tablets 60 mg are round, orange-colored, film-coated tablets bearing the symbol PF on one side and M 60 on the other. They are supplied as follows:

NDC 59011-262-10: opaque plastic bottles containing 100 tablets
NDC 59011-262-05: opaque plastic bottles containing 500 tablets

MS CONTIN® (morphine sulfate controlled-release) Tablets 100 mg are round, gray-colored, film-coated tablets bearing the symbol PF on one side and 100 on the other. They are supplied as follows:

NDC 59011-263-10: opaque plastic bottles containing 100 tablets
NDC 59011-263-05: opaque plastic bottles containing 500 tablets

MS CONTIN® (morphine sulfate controlled-release) Tablets 200 mg are capsule-shaped, green-colored, film-coated tablets bearing the symbol PF on one side and M 200 on the other. They are supplied as follows:

NDC 59011-264-10: opaque plastic bottles containing 100 tablets

STORAGE AND HANDLING

Store at 25°C (77°F); excursions permitted between 15°-30°C (59°-86°F).

Dispense in a tight, light-resistant container.

Healthcare professionals can telephone Purdue Pharma’s Medical Services Department (1-888-726-7535) for information on this product.

CAUTION

DEA Order Form Required.

Purdue Pharma L.P.
Stamford, CT 06901-3431

©2009, Purdue Pharma L.P.
March 4, 2009
301617-0B

PACKAGE LABEL

MS CONTIN CR 60MG LABEL IMAGE